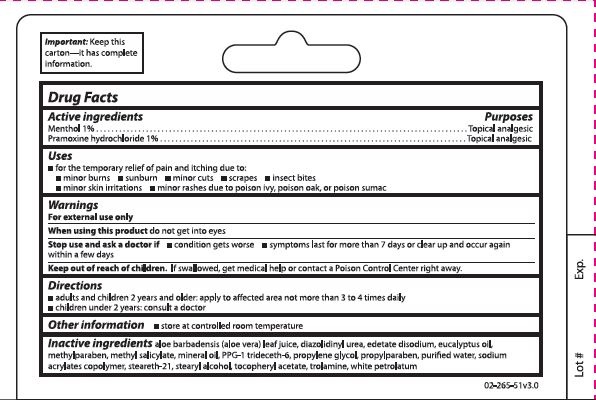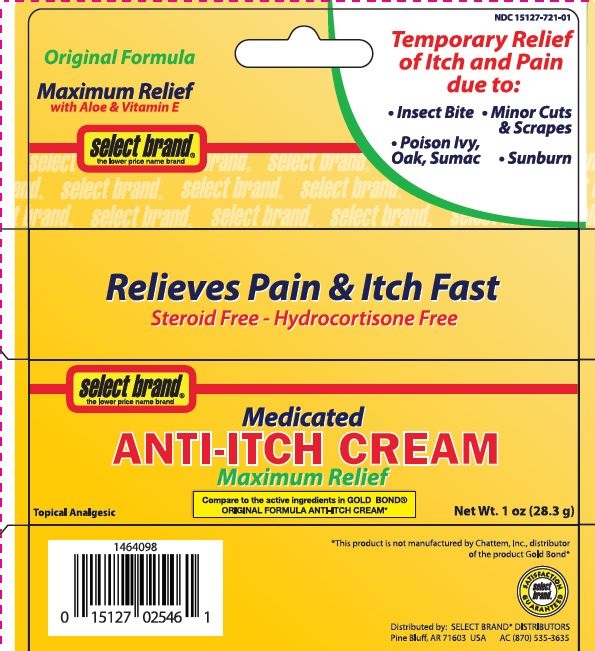 DRUG LABEL: Select Brand Anti-Itch
NDC: 15127-721 | Form: CREAM
Manufacturer: Select Brand
Category: otc | Type: HUMAN OTC DRUG LABEL
Date: 20150112

ACTIVE INGREDIENTS: PRAMOXINE HYDROCHLORIDE .1 g/10 g; MENTHOL, UNSPECIFIED FORM .1 g/10 g
INACTIVE INGREDIENTS: PROPYLPARABEN; WATER; METHYL SALICYLATE; SODIUM ACRYLATE; EDETATE DISODIUM; METHYLPARABEN; PPG-1 TRIDECETH-6; STEARYL ALCOHOL; ALOE VERA LEAF; MINERAL OIL; .ALPHA.-TOCOPHEROL ACETATE; EUCALYPTUS OIL; DIAZOLIDINYL UREA; TROLAMINE; PROPYLENE GLYCOL; PETROLATUM

Select Brand Anti-Itch

Drug Facts

Active ingredients

Menthol 1%

Pramoxine hydrochloride 1%

Purpose

Topical analgesic

Uses

for temporary relief of pain and itching due to:

- minor burns
- sunburn
- minor cuts
- scrapes
- insect bites
- minor skin irritations
- minor rashes due to poison ivy, poison oak, or poison sumac

Warnings

For external use only

When using this product

do not get into eyes

Stop use and ask a doctor if

- condition gets worse
- symptoms last more than 7 days or clear up and occur again within a few days

Keep out of reach of children.

If swallowed, get medical help or contact a Poison Control Center right away.

Directions

adults and children 2 years and older: apply to affected area not more than 3 or 4 times daily

children under 2 years: consult a doctor

Other Information

- store at controlled room temperature

Inactive ingredients

aloe barbadensis (aloe vera) leaf juice, diazolidinyl urea, edetate disodium, eucalyptus oil, methylparaben, methyl salicylate, mineral oil, PPG-1 trideceth-6, propylene glycol, propylparaben, purified water, sodium acrylates copolymer, steareth-21, stearyl alcohol, tocopheryl acetate, trolamine, white petrolatum

PRINCIPAL DISPLAY PANEL

Select Brand Medicated Anti-Itch Cream

Maximum Relief

Topical Analgesic

Net wt 1 oz (28.3 g)